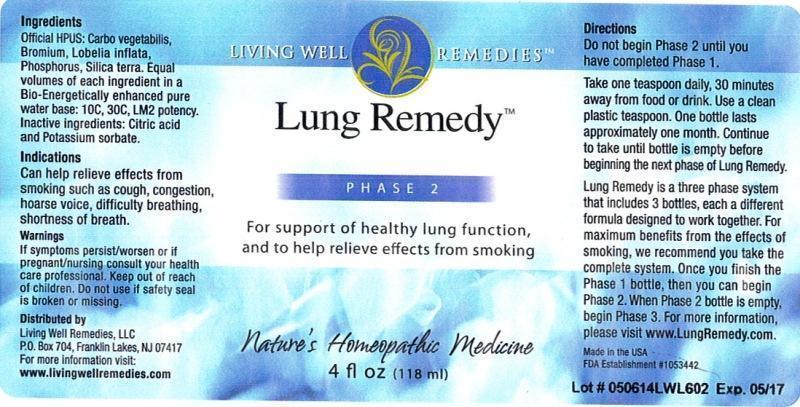 DRUG LABEL: Lung Remedy Phase 2
NDC: 53852-0003 | Form: LIQUID
Manufacturer: Living Well Remedies, LLC
Category: homeopathic | Type: HUMAN OTC DRUG LABEL
Date: 20141029

ACTIVE INGREDIENTS: ACTIVATED CHARCOAL 10 [hp_C]/118 mL; BROMINE 10 [hp_C]/118 mL; LOBELIA INFLATA 10 [hp_C]/118 mL; PHOSPHORUS 10 [hp_C]/118 mL; SILICON DIOXIDE 10 [hp_C]/118 mL
INACTIVE INGREDIENTS: WATER; CITRIC ACID MONOHYDRATE; POTASSIUM SORBATE

Lung Remedy Phase 2

ACTIVE INGREDIENT

Active Ingredients: Office HPUS: Carbo vegetabilis, Bromium, Lobelia inflata, Phosphorus, Silicea. Equal volumes of each ingredient in 10C, 30C, LM2 potency.

INACTIVE INGREDIENT

Inactive ingredients: Bio-Energetically enhanceced pure water base, Citric acid and Potassium sorbate.

PURPOSE

Indications

Can help relieve effects from smoking such as:

- cough
- congestion
- hoarse voice
- difficulty breathing
- shortness of breath

Warnings

If symptoms persist/worsen or if pregnant/nursing consult your health care professional.

Keep out of reach of children.

Do not use if safety seal is broken or missing.

DOSAGE AND ADMINISTRATION

Directions: Do not begin Phase 2 until you have completed Phase 1.

Take one teaspoon daily, 30 minutes away from food or drink. Use a clean plastic teaspoon. One bottle lasts approximately one month. Continue to take until bottle is empty before beginning the next phase of Lung Remedy.

Lung Remedy is a three phase system that includes 3 bottles, each a different formula designed to work together. For maximum benefits from the effects of smoking, we recommend you take the complete system. Once you finish the Phase 1 bottle, then you can begin Phase 2. When Phase 2 bottle is empty, begin Phase 3. For more information, please visit www.LungRemedy.com.

Indications:

Can help relieve effects from smoking such as cough, congestion, hoarse voice, difficulty breathing, shortness of breath.